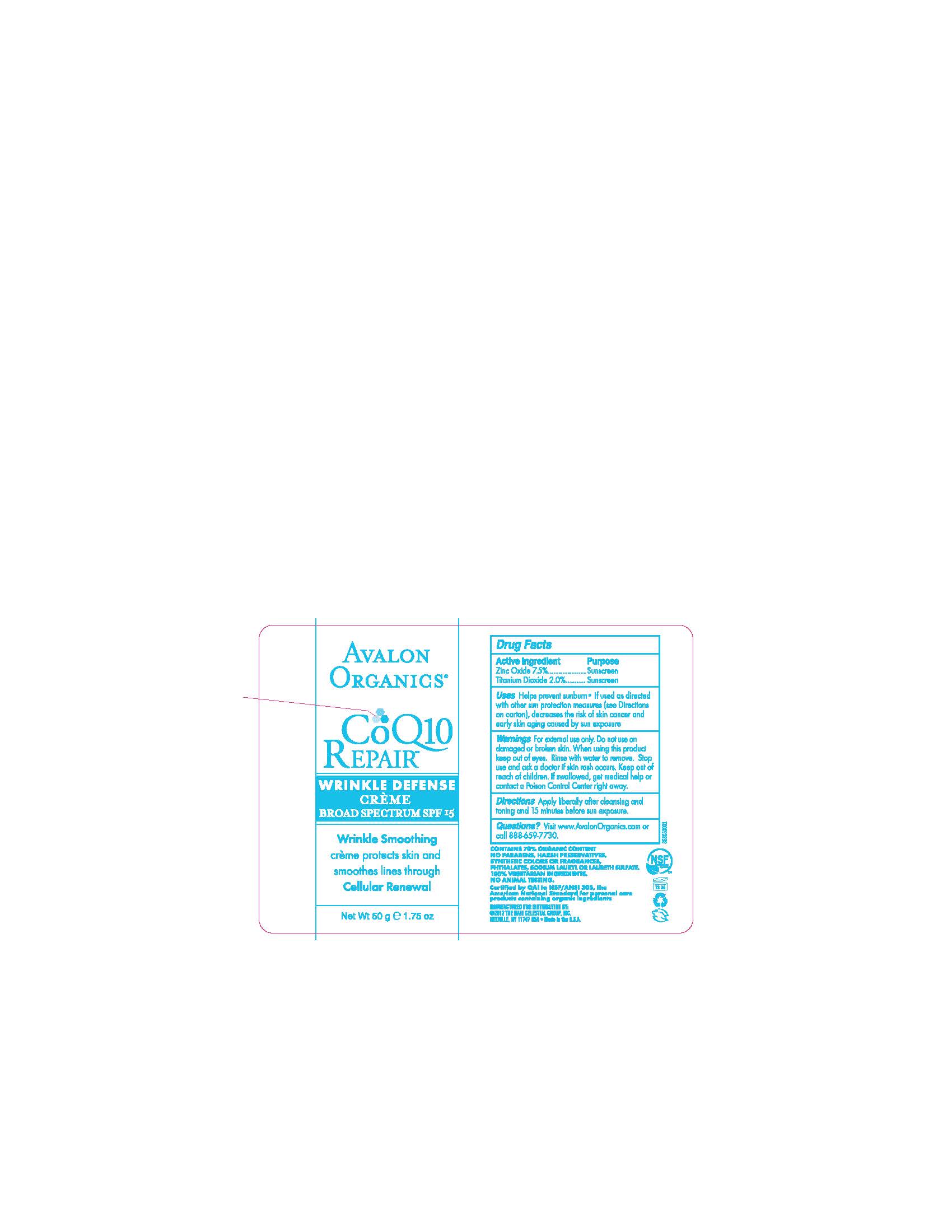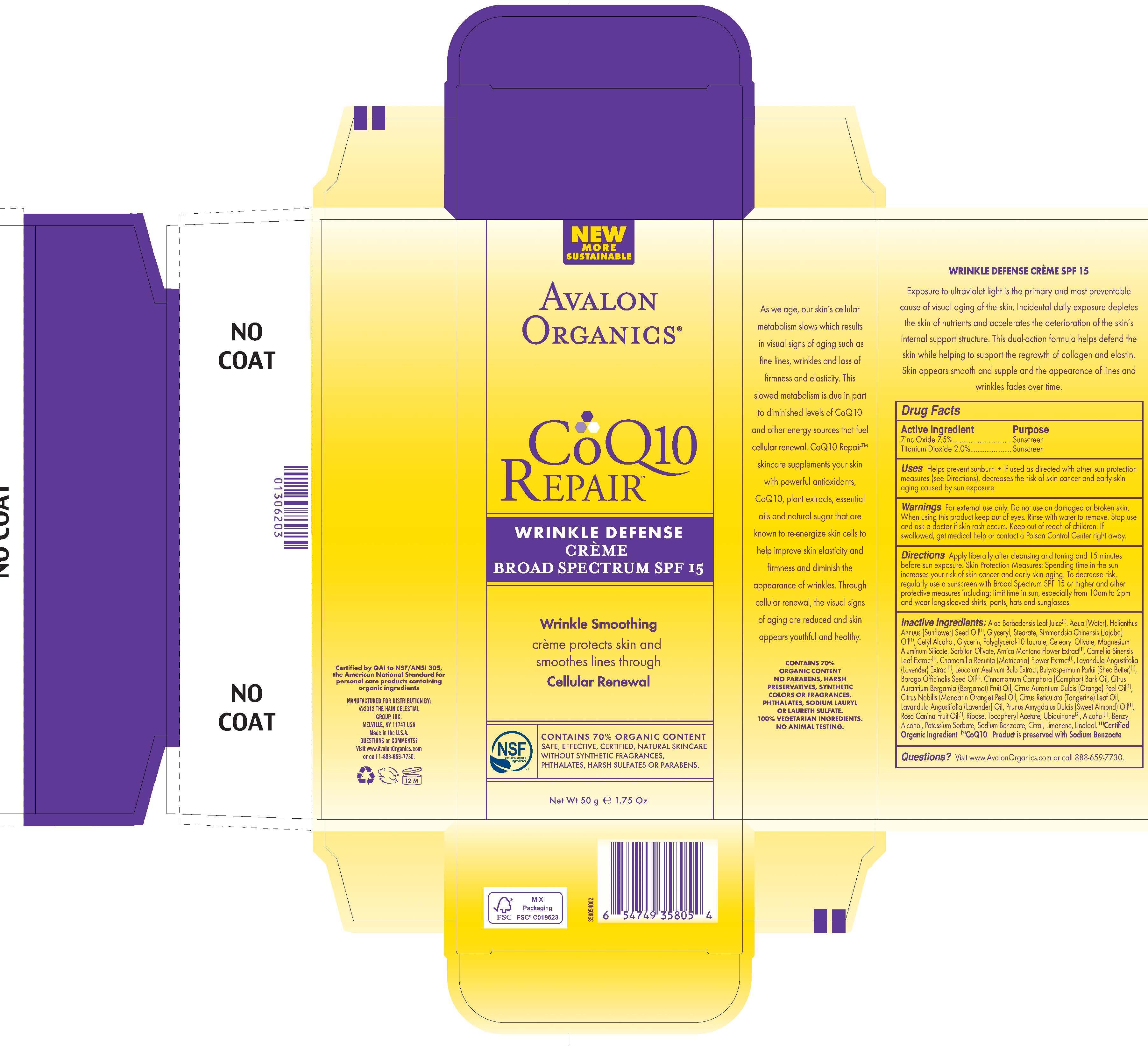 DRUG LABEL: Avalon Organics COQ10 Repair Wrinkle Defense  Broad Spectrum SPF15
NDC: 61995-1805 | Form: CREAM
Manufacturer: The Hain Celestial Group, Inc.
Category: otc | Type: HUMAN OTC DRUG LABEL
Date: 20121031

ACTIVE INGREDIENTS: ZINC OXIDE 7.5 g/100 g; TITANIUM DIOXIDE 2.0 g/100 g
INACTIVE INGREDIENTS: WATER; GLYCERYL MONOSTEARATE    ; GLYCERIN; ALOE VERA LEAF; SUNFLOWER OIL ; CETYL ALCOHOL; JOJOBA OIL; POLYGLYCERYL-10 LAURATE ; CETEARYL OLIVATE; MAGNESIUM ALUMINUM SILICATE; SORBITAN OLIVATE; BORAGE OIL; BERGAMOT OIL; ORANGE OIL    ; SHEA BUTTER    ; MANDARIN OIL    ; ROSA CANINA FRUIT OIL ; ARNICA MONTANA FLOWER; LAVENDER OIL; GREEN TEA LEAF; CHAMOMILE ; CITRUS RETICULATA LEAF OIL; CAMPHOR OIL    ; LAVANDULA ANGUSTIFOLIA FLOWER ; ALMOND OIL; RIBOSE, D-; .ALPHA.-TOCOPHEROL ACETATE; LEUCOJUM AESTIVUM BULB   ; UBIDECARENONE; POTASSIUM SORBATE; SODIUM BENZOATE; ALCOHOL ; BENZYL ALCOHOL; CITRAL ; LIMONENE, (+/-)- ; LINALOOL, (+/-)-

Drug Facts

ACTIVE INGREDIENT

Titanium Dioxide 2.0%

Zinc Oxide 7.5%

PURPOSE

Sunscreen

INDICATIONS AND USAGE

- Helps prevent sunburns
- If used as directed with other sun protection measures, decreases the risk of skin cancer and early skin aging, caused by sun exposure.

WARNINGS

For external use only. Do not use on damaged or broken skin. When using this product keep out of eyes.Rinse with water to remove. Stop use and ask a doctor if skin rash occurs.

Keep out of reach of children. If swallowed, get medical help or contact a Poison Control Center right away.

DOSAGE AND ADMINISTRATION

Apply liberally after cleansing and toning at 15 minutes before sun exposure. Skin Protection Measures: Spending time in the sun increases your risk of skin cancer and early skin aging.To decrease risk, regularly use a sunscreen with Broad Spectrum SPF 15 or higher and other protective measures including: limit time in the sun, especially from 10am to 2pm and wear long-sleeved shirts, pants, hats and sunglasses.

INACTIVE INGREDIENT

Aloe Barbadensis Leaf Juice (1), Aqua (Water), Helianthus Annuus (Sunflower) Seed Oil (1), Simmondsia Chinensis (Jojoba) Seed Oil (1), Glyceryl Stearate, Cetyl Alcohol, Glycerin, Polyglycerol-10 Laurate, Cetearyl Olivate, Magnesium Aluminum Silicate, Sorbitan Olivate, Arnica Montana Flower Extract (1),Camellia Sinenensis Leaf Extract (1), Chamomilla Recutita (Matricaria) Flower Extract (1), Lavandula Angustifolia (Lavender) Flower Extract (1), Leucojum Aestivum Bulb Extracr, Butyrospermum Parkii (Shea) Butter (1),Borage Officinalis Seed Oil (1), Cinnamomum Camphora (Camphor) Bark Oil, Citrus Aurantium Bergamia (Bergamot) Fruit Oil, Citrus Aurantium Dulcis (Orange) Peel Oil, Citrus Nobilis (Mandarin Orange) Peel Oil, Citrus Reticulata (Tangerine) Leaf Oil,Lavandula Angustifolia (Lavender) Oil,Prunus Amygdalus Dulcis (Sweet Almond) Oil (1), Rosa Canina Fruit Oil (1), Ribose, Tocopheryl Acetate, Ubiquinone, Alcohol (1), Benzyl Alcohol, Potassium Sorbate, Sodium Benzoate, Citral, Limonene, Linalool.

(1) Certified Organic Ingredients

QUESTIONS

Questions? Visit AvalonOrganics.com or call (888) 659-7730.